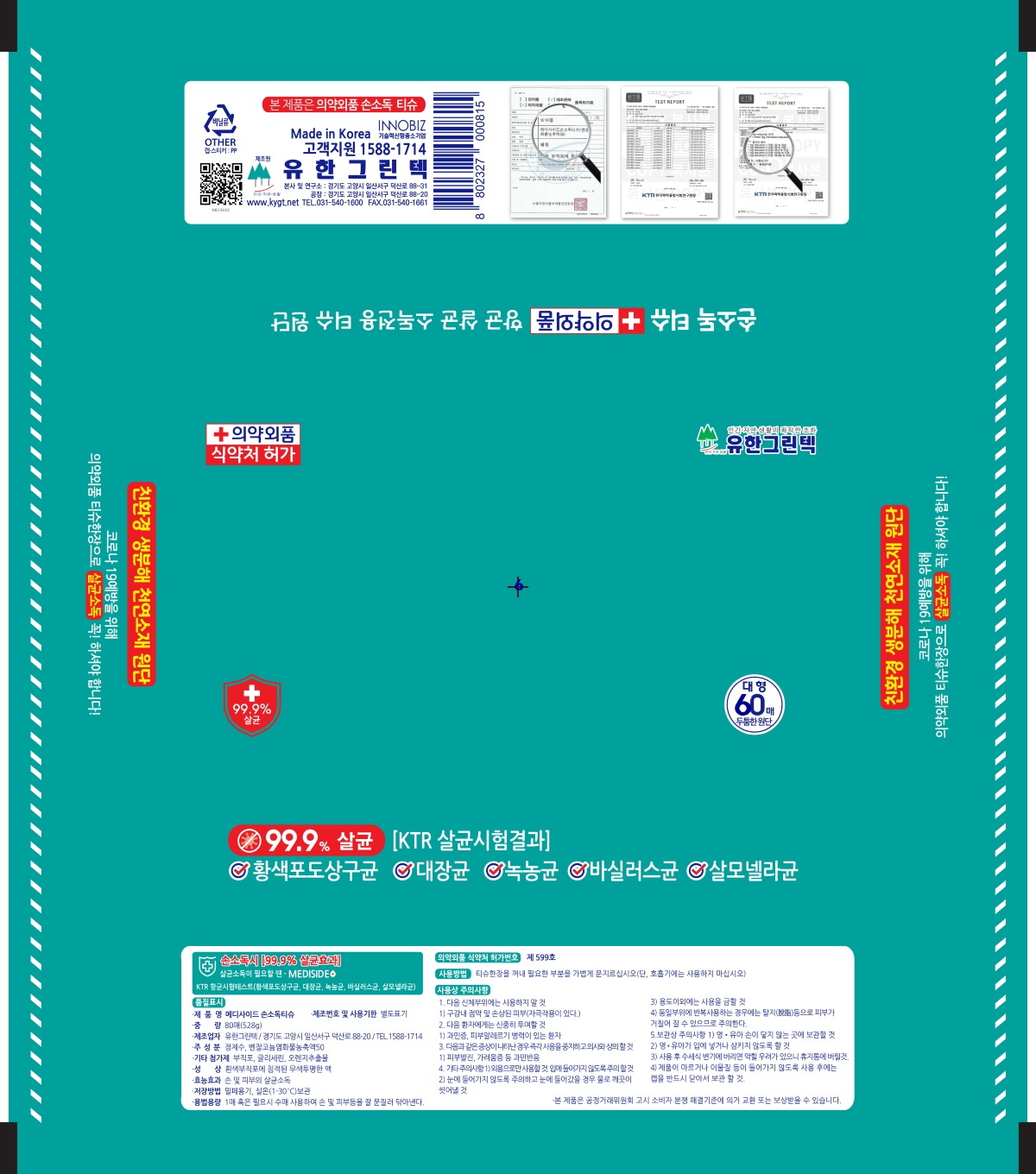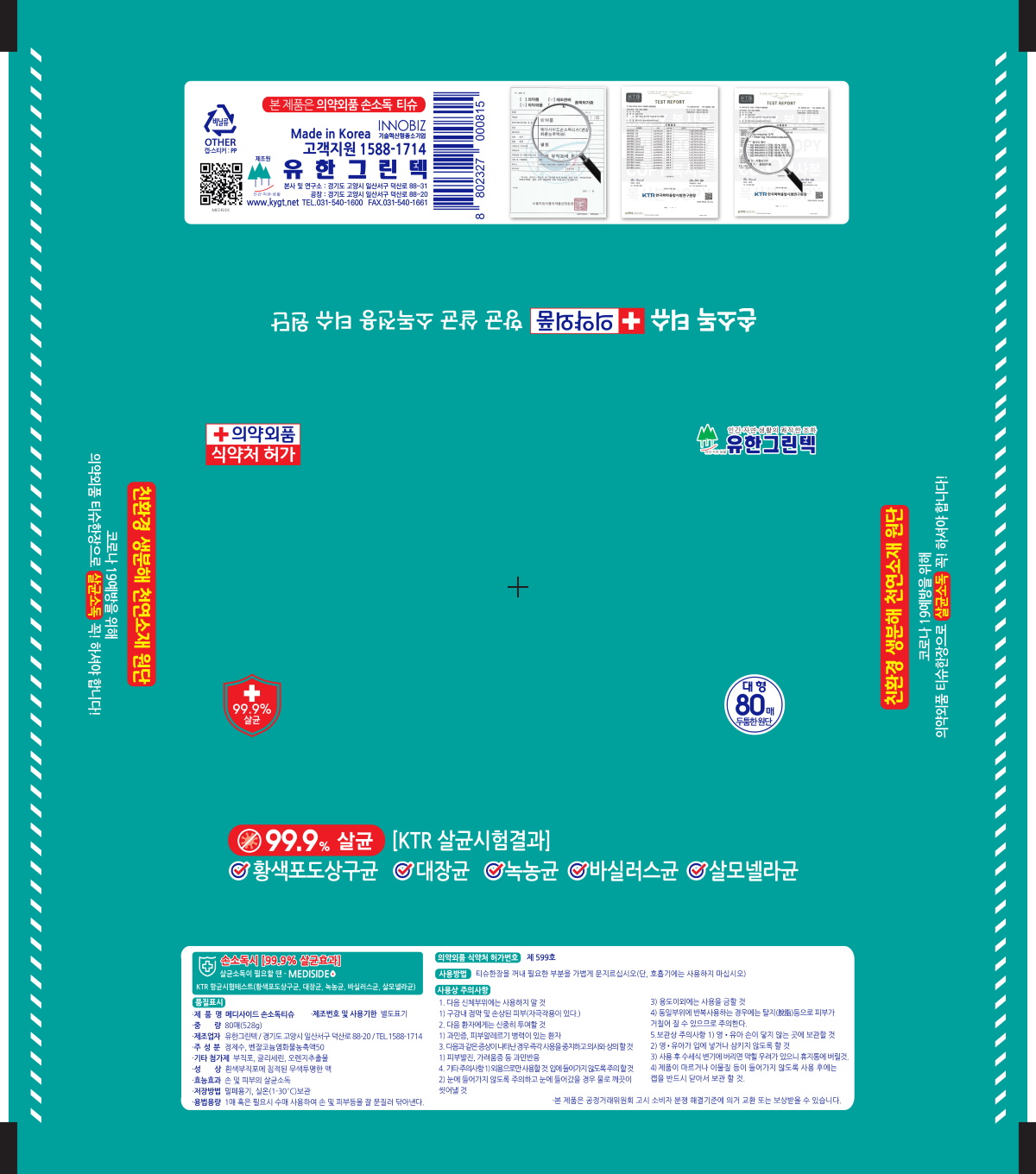 DRUG LABEL: MEDISIDE-HAND ANTISEPTIC TISSUE
NDC: 78583-702 | Form: LIQUID
Manufacturer: YOU HAN GREENTECH
Category: otc | Type: HUMAN OTC DRUG LABEL
Date: 20220705

ACTIVE INGREDIENTS: BENZALKONIUM CHLORIDE 0.1 g/100 g
INACTIVE INGREDIENTS: GLYCERIN; ORANGE OIL; WATER

78583-702

ACTIVE INGREDIENT

BENZALKONIUM CHLORIDE 0.1%

PURPOSE

ANTIMICROBIAL

Direction

To dispense, peel back front label at tab

Remove towelettes as needed

Reseal pouch by pressing label firmly back into place

Do not use

do not flush

do not use if you are allergic to any of the ingredients

Warnings

for external sue only.

sotre away from direct sunlight or high temperature.

use caution near electric appliances to avoid electric shock.

Keep out of reach of children.

stop use and ask a doctor if irritationor or rash edvelopes and continues for more than 72 hours.

Use

peel back front label slowy.

use caution near electric appliances to avoid electric shock

ask a doctor

f swallowed, get medical help or contact a Poison control center right away

Other information

7.9 in x 5.9 in (20cm x15cm)

INACTIVE INGREDIEINT

Aqua

Glycerine

Orange Sweet Ext.